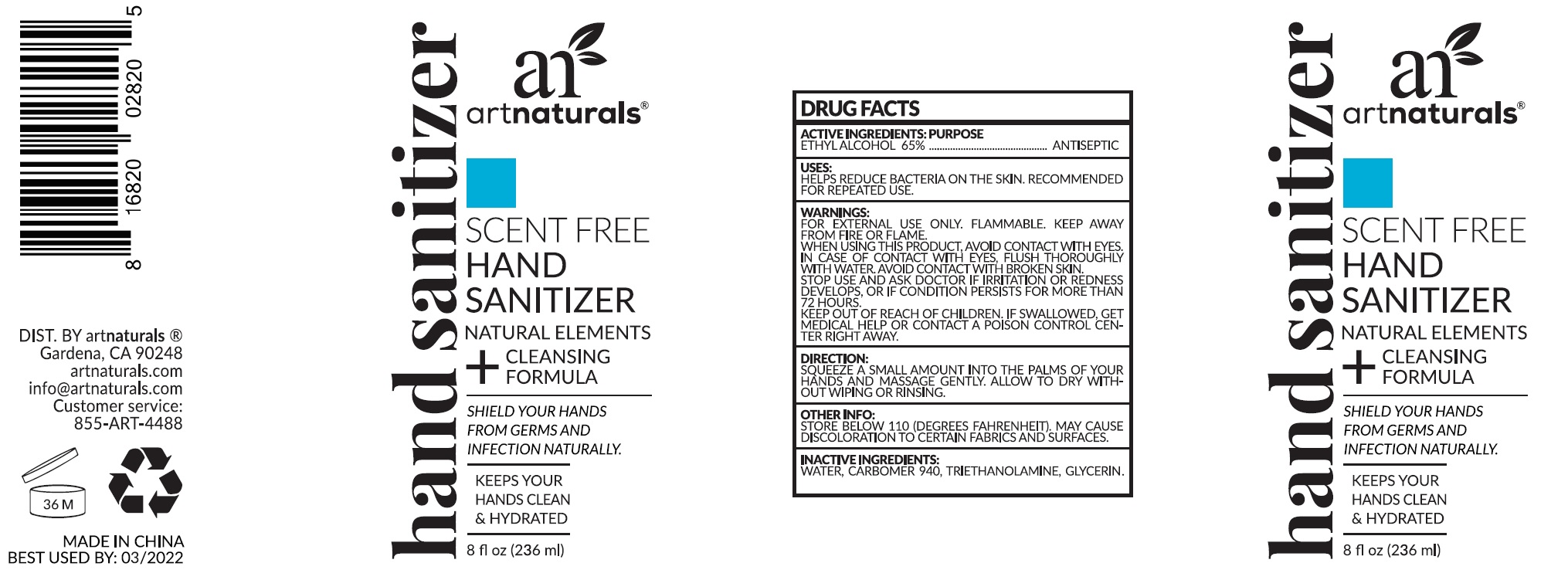 DRUG LABEL: Art Naturals Hand Sanitizer
NDC: 78706-000 | Form: GEL
Manufacturer: Virgin Scent Inc.
Category: otc | Type: HUMAN OTC DRUG LABEL
Date: 20220721

ACTIVE INGREDIENTS: ALCOHOL 0.65 mL/1 mL
INACTIVE INGREDIENTS: WATER; CARBOMER HOMOPOLYMER TYPE C (ALLYL PENTAERYTHRITOL CROSSLINKED); TROLAMINE; GLYCERIN

Art Naturals Hand Sanitizer

ACTIVE INGREDIENTS:

ETHYL ALCOHOL 65%

PURPOSE

ANTISEPTIC

USES:

HELPS REDUCE BACTERIA ON THE SKIN. RECOMMENDED FOR REPEATED USE.

WARNINGS:

FOR EXTERNAL USE ONLY. FLAMMABLE. KEEP AWAY FROM FIRE OR FLAME.

WHEN USING THIS PRODUCT,

AVOID CONTACT WITH EYES. IN CASE OF CONTACT WITH EYES, FLUSH THOROUGHLY WITH WATER AVOID CONTACT WITH BROKEN SKIN.

STOP USE AND ASK DOCTOR

IF IRRITATION OR REDNESS DEVELOPS, OR IF CONDITION PERSISTS FOR MORE THAN 72 HOURS.

KEEP OUT OF REACH OF CHILDREN.

IF SWALLOWED, GET MEDICAL HELP OR CONTACT A POISON CONTROL CENTER RIGHT AWAY.

DIRECTION:

SQUEEZE A SMALL AMOUNT INTO THE PALMS OF YOUR HANDS AND MASSAGE GENTLY. ALLOW TO DRY WITHOUT WIPING OR RINSING.

OTHER INFO:

STORE BELOW 110 (DEGREES FAHRENHEIT). MAY CAUSE DISCOLORATION TO CERTAIN FABRICS AND SURFACES.

INACTIVE INGREDIENTS:

WATER, CARBOMER 940, TRIETHANOLAMINE, GLYCERIN.